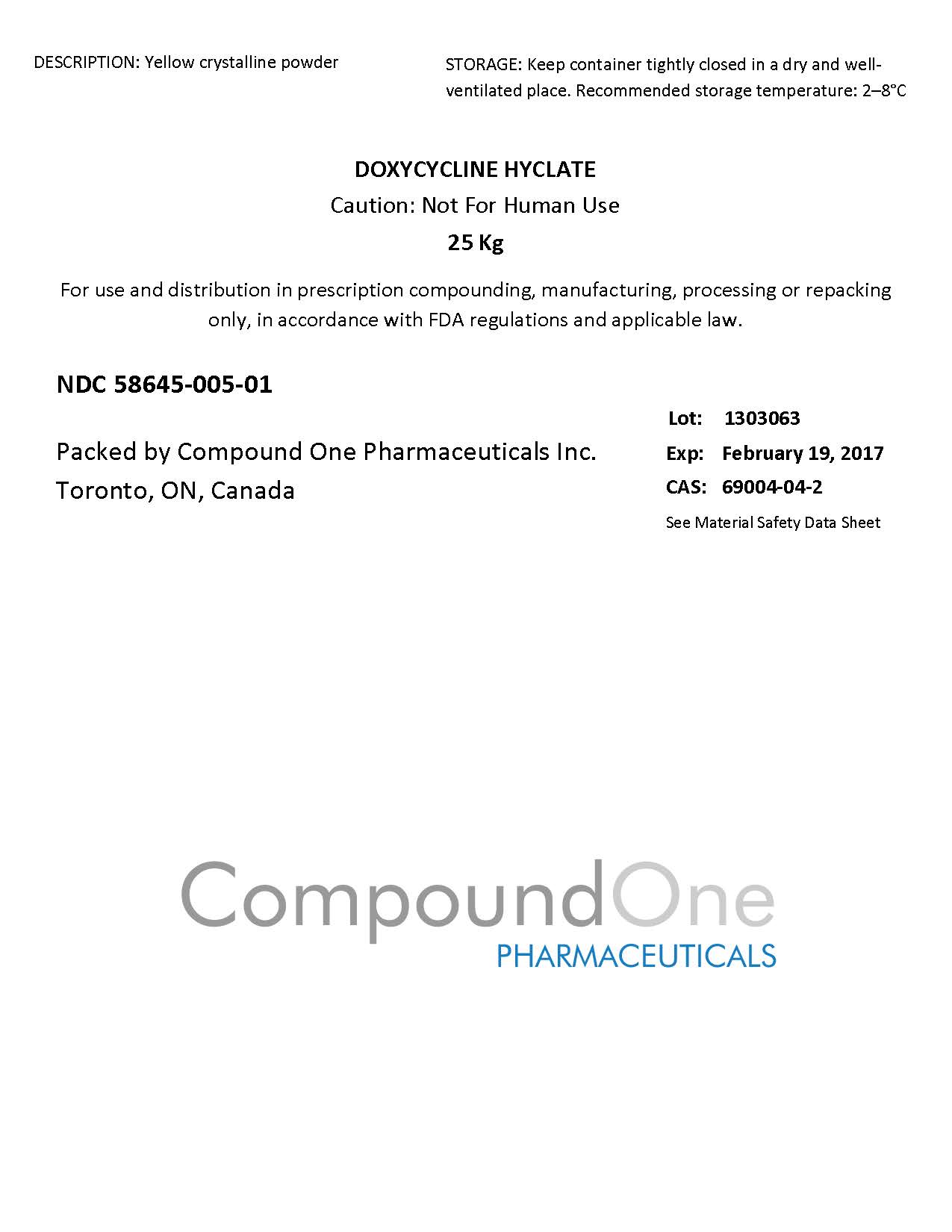 DRUG LABEL: Doxycycline Hyclate
                
                
NDC: 58645-005 | Form: POWDER
Manufacturer: Compound One Pharmaceuticals Inc
Category: other | Type: BULK INGREDIENT
Date: 20140205

ACTIVE INGREDIENTS: DOXYCYCLINE HYCLATE 1 g/1 g

Drug Facts